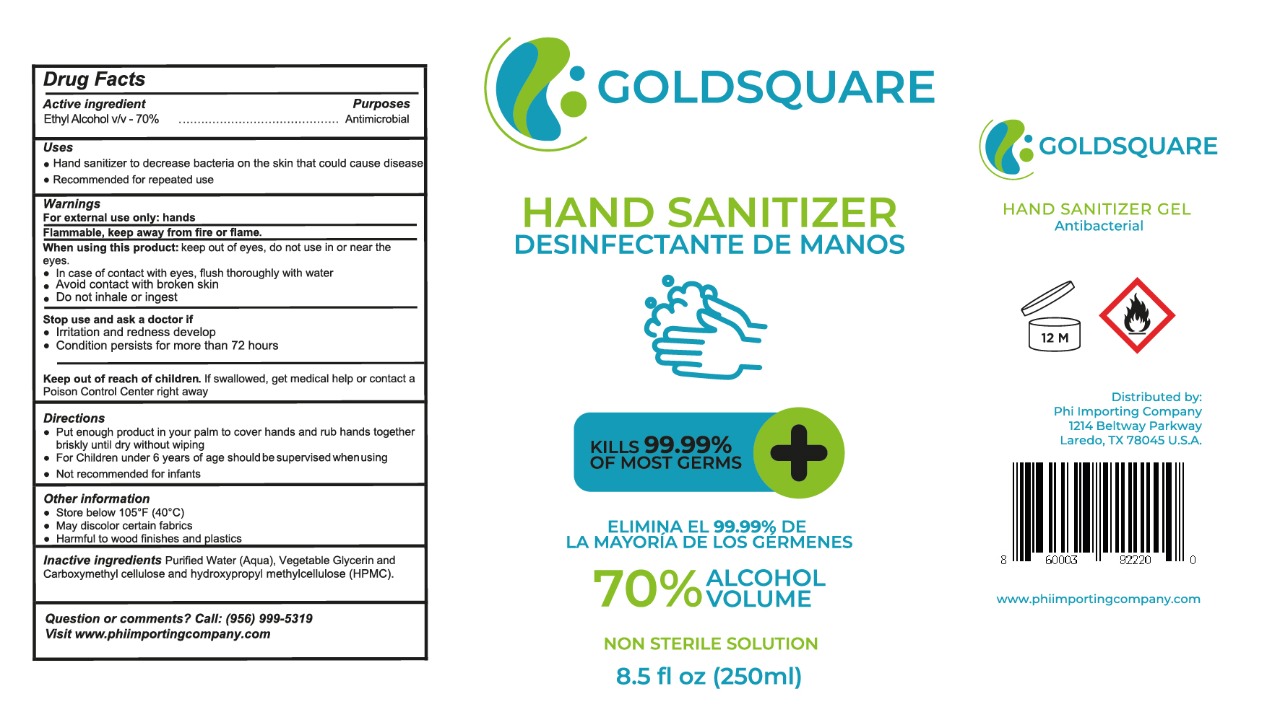 DRUG LABEL: HAND SANITIZER
NDC: 77210-0007 | Form: GEL
Manufacturer: EXPORTADORA IN & OUT S DE RL DE CV
Category: otc | Type: HUMAN OTC DRUG LABEL
Date: 20200610

ACTIVE INGREDIENTS: ALCOHOL 70 mL/100 mL
INACTIVE INGREDIENTS: HYPROMELLOSE 2208 (60000 MPA.S) 0.1 mL/100 mL; WATER 29.6 mL/100 mL; GLYCERIN 0.2 mL/100 mL; CARBOXYMETHYLCELLULOSE 0.1 mL/100 mL

Active ingredient

Ethyl alcohol v/v - 70%

Purposes

Antimicrobial

Uses

- Hand sanitizer to decrase bacteria on the skin that could cause disease

- Recommended for repeted use

Warnings

For external use only: hands

Flammable, keep away form fire or flame

When using this product

keep out of eyes, do not use in or near the eyes

-in case of contact eyes, flush thorougly with water

-Avoid contact with broken skin

-Do not inhale or ingest

When using this product

keep out of eyes, do not use in or near the eyes

-in case of contact eyes, flush thorougly with water

-Avoid contact with broken skin

-Do not inhale or ingest

Stop use and ask a doctor if

-irritation and redness develop

-condition persists for more than 72 hours

keep out of reach of children

if swallowed, get medical help or contact a posion center right away

directions

-Put enough product in your palm to cover hands and rub hands together briskly until dry without wiping

-For children under 6 years of age should be supervised when using

-Not recommended for infants

Other information

- Store below 105 F (40 C)

- May discolor certain fabrics

- Harmful to wood finishes and plastics

Inactive ingredients

Purified water (aqua), Vegetable glycerin and carboxymethyl cellulose and hydroxypropyl methylcellulose HPMC

QUESTION OR COMMENTS

CALL: 956 999 5319

visit www.phiimportingcompany.com

PRINCIPAL DISPLAY

hand sanitizer

desifectante para manos

kills 99.9% of most germs

elima el 99.9% de la mayoria de germenes

70% alcohol volume

non sterile solution

8.5 fl oz (250 ml)